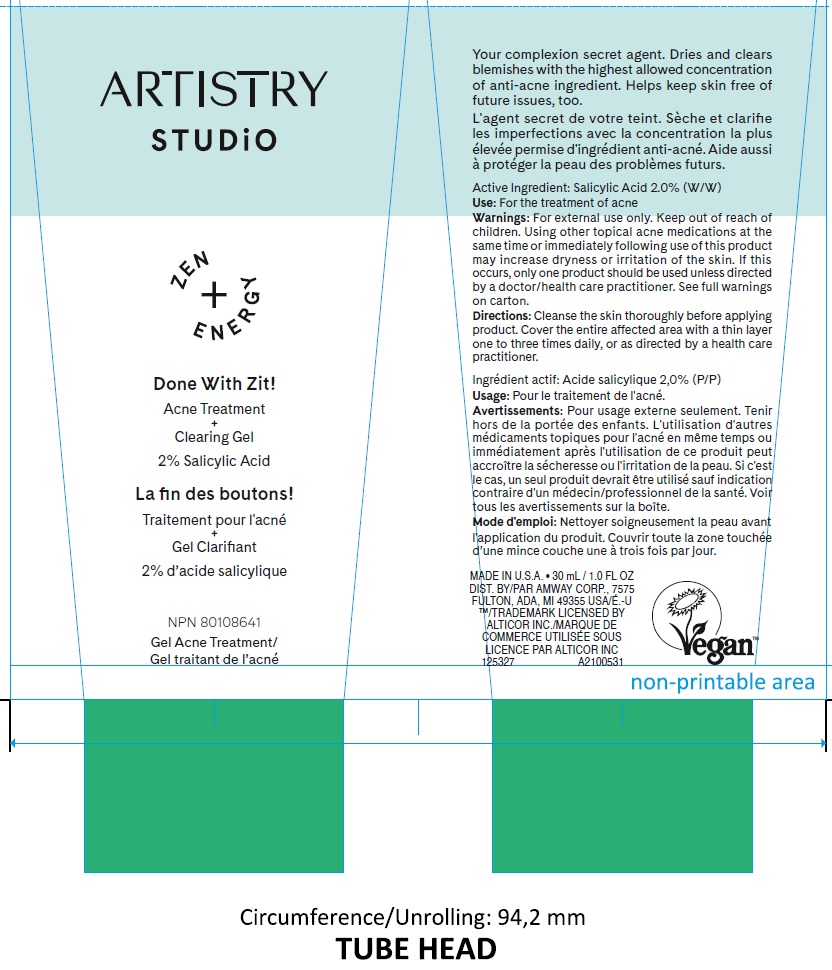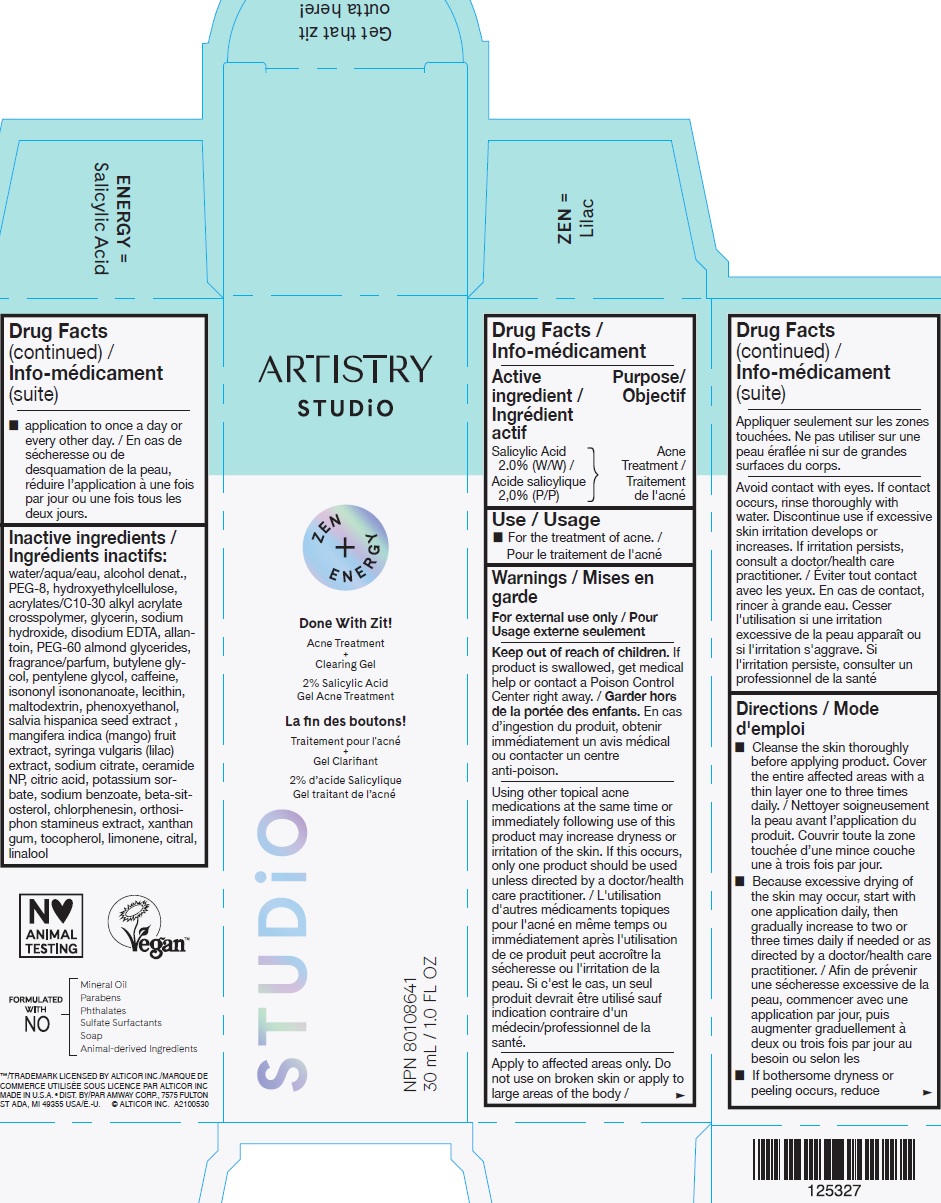 DRUG LABEL: Artistry Studio Done With Zit Acne Treatment Clearing Gel
NDC: 10056-045 | Form: GEL
Manufacturer: Access Business Group LLC
Category: otc | Type: HUMAN OTC DRUG LABEL
Date: 20231021

ACTIVE INGREDIENTS: SALICYLIC ACID 20 mg/1 mL
INACTIVE INGREDIENTS: WATER; ALCOHOL; POLYETHYLENE GLYCOL 400; HYDROXYETHYL CELLULOSE, UNSPECIFIED; CARBOMER INTERPOLYMER TYPE A (ALLYL SUCROSE CROSSLINKED); GLYCERIN; SODIUM HYDROXIDE; EDETATE DISODIUM ANHYDROUS; ALLANTOIN; PEG-60 ALMOND GLYCERIDES; BUTYLENE GLYCOL; PENTYLENE GLYCOL; CAFFEINE; ISONONYL ISONONANOATE; MALTODEXTRIN; PHENOXYETHANOL; CHIA SEED; MANGO; SODIUM CITRATE; CERAMIDE NP; CITRIC ACID MONOHYDRATE; POTASSIUM SORBATE; SODIUM BENZOATE; .BETA.-SITOSTEROL; CHLORPHENESIN; XANTHAN GUM; TOCOPHEROL; LIMONENE, (+)-; CITRAL; LINALOOL, (+/-)-

Artistry Studio Done With Zit! Acne Treatment + Clearing Gel

Active ingredient

Salicylic Acid 2.0% (W/W)

Purpose

Acne Treatment

Use

- For the treatment of acne.

Warnings

For external use only

Keep out of reach of children.

If product is swallowed, get medical help or contact a Poison Control Center right away.

Using other topical acne medications at the same time or immediately following use of this product may increase dryness or irritation of the skin. If this occurs, only one product should be used unless directed by a doctor/health care practitioner.

Apply to affected areas only. Do not use on broken skin or apply tolarge areas of the body

Avoid contact with eyes. If contact occurs, rinse thoroughly with water. Discontinue use if excessive skin irritation develops or increases. If irritation persists, consult a doctor/health care practitioner.

Directions

- Cleanse the skin thoroughly before applying product. Cover the entire affected areas with a thin layer one to three times daily.
- Because excessive drying of the skin may occur, start with one application daily, then gradually increase to two or three times daily if needed or as directed by a doctor/health care practitioner.
- If bothersome dryness or peeling occurs, reduce application to once a day or every other day.

Inactive ingredients

water/aqua/eau, alcohol denat., PEG-8, hydroxyethylcellulose, acrylates/C10-30 alkyl acrylate crosspolymer, glycerin, sodium hydroxide, disodium EDTA, allantoin, PEG-60 almond glycerides, fragrance/parfum, butylene glycol, pentylene glycol, caffeine, isononyl isononanoate, lecithin, maltodextrin, phenoxyethanol, salvia hispanica seed extract, mangifera indica (mango) fruit extract, syringa vulgaris (lilac) extract, sodium citrate, ceramide NP, citric acid, potassium sorbate, sodium benzoate, beta-sitosterol, chlorphenesin, orthosiphon stamineus extract, xanthan gum, tocopherol, limonene, citral, linalool